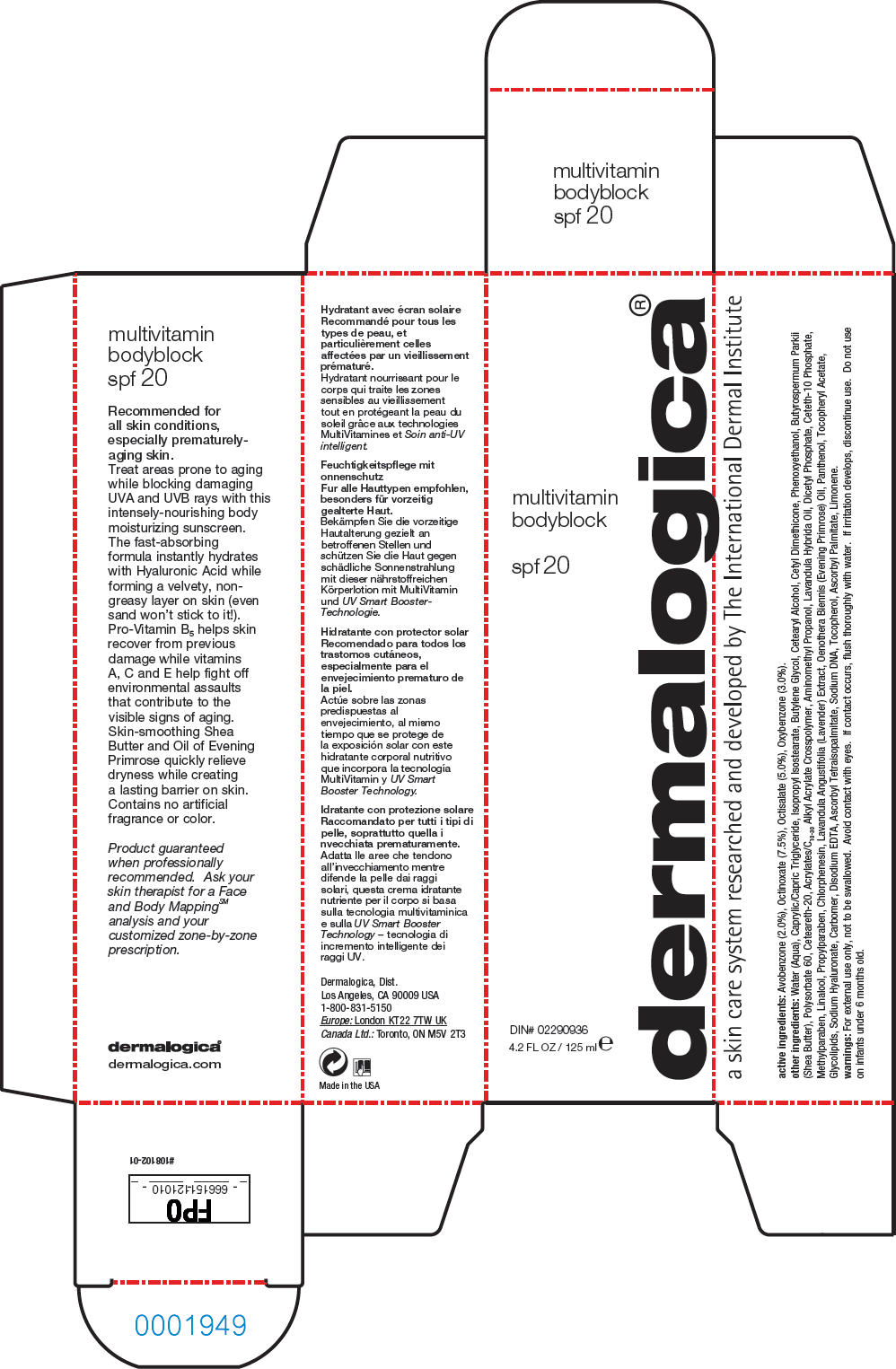 DRUG LABEL: Multivitamin Bodyblock 
NDC: 21839-101 | Form: LOTION
Manufacturer: Gordon Laboratories, Inc
Category: otc | Type: HUMAN OTC DRUG LABEL
Date: 20120119

ACTIVE INGREDIENTS: Avobenzone 2.5 mL/125 mL; Octinoxate 9.4 mL/125 mL; Octisalate 6.25 mL/125 mL; Oxybenzone 3.75 mL/125 mL
INACTIVE INGREDIENTS: Water; Medium-Chain Triglycerides; Isopropyl Isostearate; Butylene Glycol; Cetostearyl Alcohol; Phenoxyethanol; Shea Butter; Polysorbate 60; Polyoxyl 20 Cetostearyl Ether; Aminomethylpropanol; Lavandin Oil; Dihexadecyl Phosphate; Ceteth-10 Phosphate; Methylparaben; Linalool, (+/-)-; Propylparaben; Chlorphenesin; Lavandula Angustifolia Flowering Top; Evening Primrose Oil; Panthenol; Alpha-Tocopherol Acetate; Hyaluronate Sodium; Edetate Disodium; Tocopherol; Ascorbyl Palmitate

dermalogica®
multivitamin
bodyblock
spf 20

active ingredients

Avobenzone (2.0%), Octinoxate (7.5%), Octisalate (5.0%), Oxybenzone (3.0%).

other ingredients

Water, Caprylic/Capric Triglyceride, Isopropyl Isostearate, Butylene Glycol, Cetearyl Alcohol, Cetyl Dimethicone, Phenoxyethanol, Butyrospermum Parkii (Shea Butter), Polysorbate 60, Ceteareth-20, Acrylates/C10-30 Alkyl Acrylate Crosspolymer, Aminomethyl Propanol, Lavandula Hybrida Oil, Dicetyl Phosphate, Ceteth-10 Phosphate, Methylparaben, Linalool, Propylparaben, Chlorphenesin, Lavandula Angustifolia (Lavender) Extract, Oenothera Biennis (Evening Primrose) Oil, Panthenol, Tocopheryl Acetate, Glycolipids, Sodium Hyaluronate, Carbomer, Disodium EDTA, Ascorbyl Tetraisopalmitate, Sodium DNA, Tocopherol, Ascorbyl Palmitate, Limonene.

warnings

For external use only, not to be swallowed.

WHEN USING

Avoid contact with eyes. If contact occurs, flush thoroughly with water.

If irritation develops, discontinue use.

Do not use on infants under 6 months old.

Dermalogica, Dist.
Los Angeles, CA 90009 USA

PRINCIPAL DISPLAY PANEL - 125 ml Tube Box

multivitamin
bodyblock

spf 20

DIN# 02290936

4.2 FL OZ / 125 ml e

dermalogica®